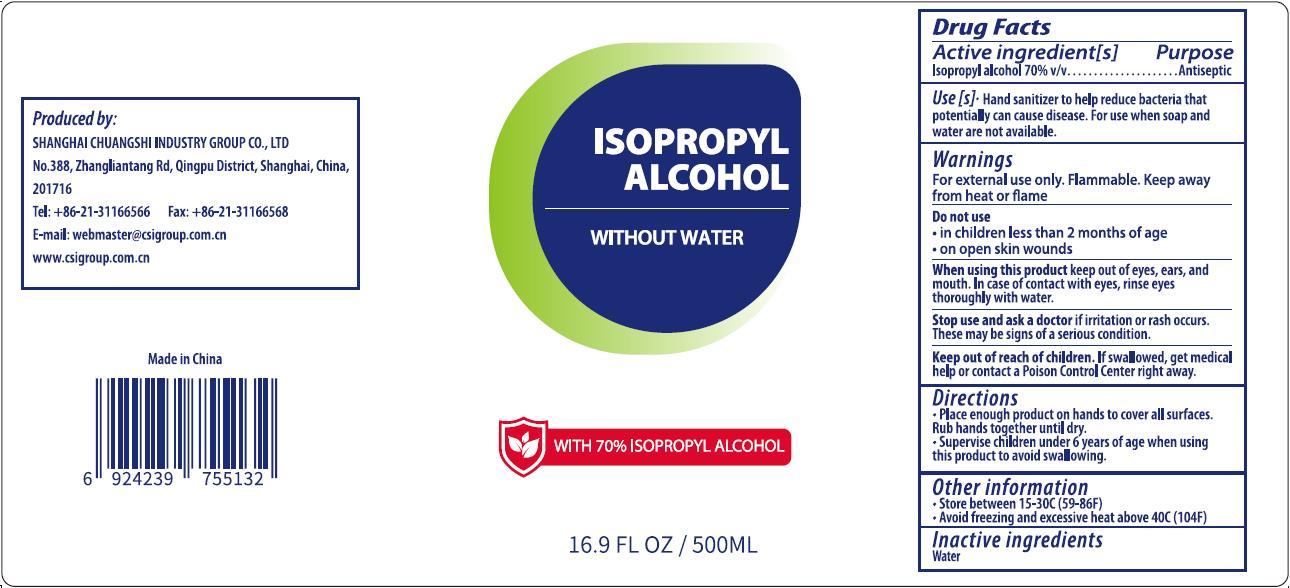 DRUG LABEL: ISOPROPYL ALCOHOL
NDC: 73557-287 | Form: LIQUID
Manufacturer: Shanghai Chuangshi Industry Group Co., Ltd
Category: otc | Type: HUMAN OTC DRUG LABEL
Date: 20200903

ACTIVE INGREDIENTS: ISOPROPYL ALCOHOL 350 mL/500 mL
INACTIVE INGREDIENTS: WATER

CSI, Hand Sanitizer, Liquid, Isopropyl Alcohol 70%; 500mL

Active Ingredient(s)

Isopropyl alcohol 70% v/v. Purpose: Antiseptic

Purpose

Antiseptic

Use(s)

Hand sanitizer to help reduce bacteria that potentially can cause disease. For use when soap and water are not available.

Warnings

For external use only. Flammable. Keep away from heat or flame.

Do not use

- in children less than 2 months of age
- on open skin wounds

When using this product keep out of eyes, ears, and mouth. If case of contact with eyes, rinse eyes thoroughly with water.

Stop use and ask a doctor if irritation or rash occurs.

These may be signs of a serious condition.

Keep out of reach of children. If swallowed, get medical help or contact a Poison Control Center right away.

Directions

- Place enough product hands to cover all surfaces. Rub hands together until dry.
- Supervise children under 6 years of age when using this product to avoid swallowing.

Other information

- Store between 15-30℃ (59-86℉)
- Avoid freezing and excessive heat above 40℃ (104℉)

Inactive ingredients

Water